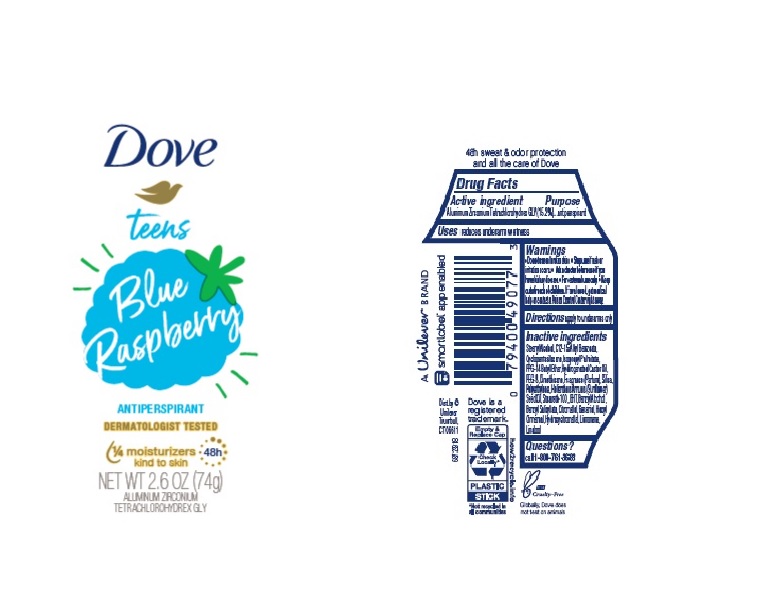 DRUG LABEL: Dove
NDC: 64942-1982 | Form: STICK
Manufacturer: Conopco Inc. d/b/a/ Unilever
Category: otc | Type: HUMAN OTC DRUG LABEL
Date: 20241108

ACTIVE INGREDIENTS: ALUMINUM ZIRCONIUM TETRACHLOROHYDREX GLY 15.2 g/100 g
INACTIVE INGREDIENTS: DIMETHICONE; PPG-14 BUTYL ETHER; STEARYL ALCOHOL; SUNFLOWER OIL; ALKYL (C12-15) BENZOATE; CYCLOMETHICONE 5; STEARETH-100; BENZYL ALCOHOL; ISOPROPYL PALMITATE; LIMONENE, (+)-; .BETA.-CITRONELLOL, (R)-; .ALPHA.-HEXYLCINNAMALDEHYDE; LINALOOL, (+/-)-; HIGH DENSITY POLYETHYLENE; HYDROGENATED CASTOR OIL; BUTYLATED HYDROXYTOLUENE; GERANIOL; HYDROXYCITRONELLAL; POLYETHYLENE GLYCOL 400; SILICON DIOXIDE; BENZYL SALICYLATE

Dove Teens Blue Raspberry 48h Antiperspirant

Drug Facts

Active ingredient

Aluminum Zirconium Tetrachlorohydrex GLY (15.2 %)

Purpose

antiperspirant

Uses

reduces underarm wetness

Warnings

• Do not use on broken skin
• Stop use if rash or irritation occurs
• Ask a doctor before use if you have kidney disease

• Keep out of reach of children.

If swallowed, get medical help or contact a Poison Control Center right away.

Directions

apply to underarms only

Inactive ingredients

Stearyl Alcohol, C12-15 Alkyl Benzoate, Cyclopentasiloxane, Isopropyl Palmitate, PPG-14 Butyl Ether, Hydrogenated Castor Oil, PEG-8, Dimethicone, Fragrance (Parfum), Silica, Polyethylene, Helianthus Annuus (Sunflower) Seed Oil, Steareth-100, BHT, Benzyl Alcohol, Benzyl Salicylate, Citronellol, Geraniol, Hexyl Cinnamal, Hydroxycitronellal, Limonene, Linalool

Questions?

Call 1-800-761-3683